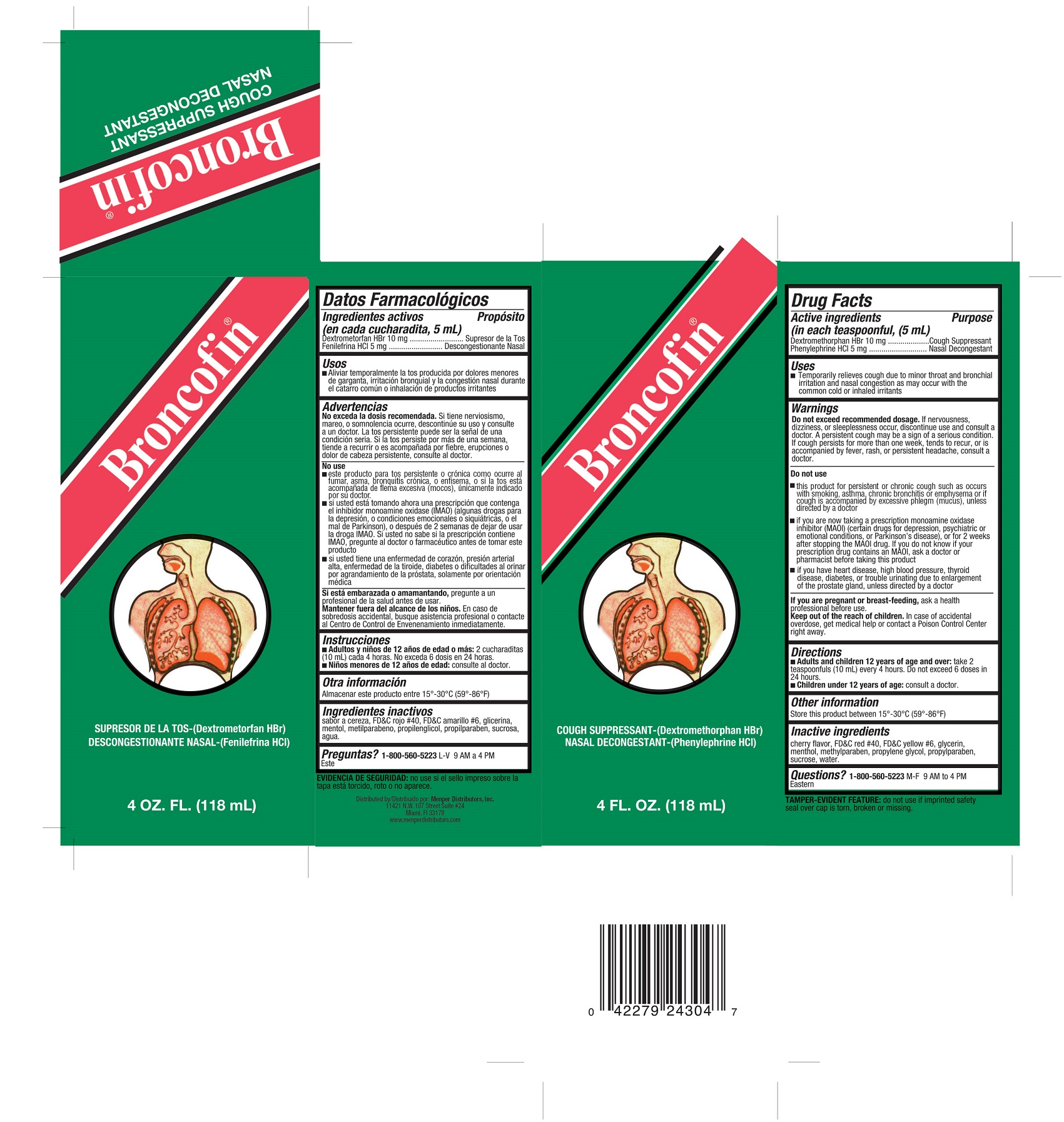 DRUG LABEL: Broncofin
NDC: 53145-026 | Form: LIQUID
Manufacturer: Menper Distributors, Inc.
Category: otc | Type: HUMAN OTC DRUG LABEL
Date: 20250722

ACTIVE INGREDIENTS: DEXTROMETHORPHAN HYDROBROMIDE 10 mg/5 mL; PHENYLEPHRINE HYDROCHLORIDE 5 mg/5 mL
INACTIVE INGREDIENTS: GLYCERIN; MENTHOL; METHYLPARABEN; PROPYLENE GLYCOL; PROPYLPARABEN; WATER; SUCROSE

Broncofin

Active Ingredients (in each teaspoonful, (5mL)

Dextromethorphan HBr 10 mg

Phenylephrine HCI 5 mg

Purpose

Cough suppressant

Nasal decongestant

Uses

Temporarily relieves cough due to minor throat and bronchial irritation and nasal congestion as may occur with the common cold or inhaled irritants

Do not exceed recommended dosage.

If nervousness, dizziness, or sleepiness occur, discontinue use and consult a doctor. A persistent cough may be a sign of a serious condition. If cough persists more than one week, tends to recur, or is accompanied by fever, rash, or persistent headache, consult a doctor.

Do not use

- this product for persistent or chronic cough such as occurs with smoking, asthma, chronic bronchitis or emphysema or if cough is accompanied by excessive phlegm (mucus), unless directed by a doctor
- if you are now taking a prescription monoamine oxidase inhibitor (MAOI) (certain drugs for depression, psychiatric or emotional conditions, or Parkinson’s disease), or for 2 weeks after stopping the MAOI drug. If you do not know if your prescription drug contains an MAOI, ask a doctor or pharmacist before taking this product
- if you have heart disease, high blood pressure, thyroid disease, diabetes, or trouble urinating due to enlargement of the prostate gland, unless directed by a doctor

If you are pregnant or breast-feeding

ask a health professional before use.

Keep out of reach of children.

In case of accidental overdose, get medical help or contact a Poison Control Center right away.

Directions

Adults and children 12 years of age and over: take 2 teaspoons (10 mL) every 4 hours. Do not exceed 6 doses in 24 hours.

Children under 12 years of age: consult a doctor.

Other information

Store this product between 15°-30°C (59°-86°F)

Inactive ingredients

cherry flavor, FD&C red #40, FD&C yellow #6, glycerin, menthol, methylparaben, propylene glycol, propylparaben, sucrose, water

Questions?

call 1-800-560-5223 M-F 9 AM to 4 PM Eastern